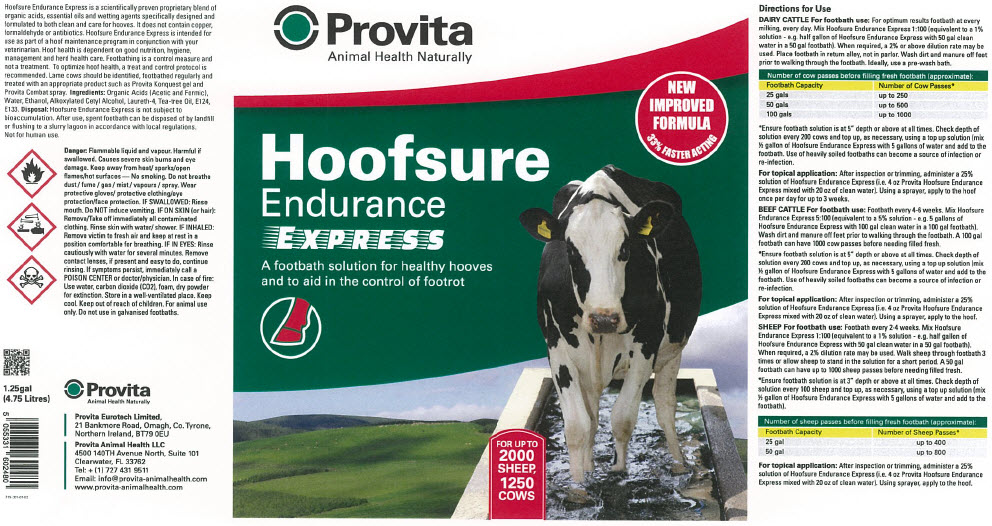 DRUG LABEL: Provita Hoofsure Endurance Express
NDC: 16371-107 | Form: SOLUTION, CONCENTRATE
Manufacturer: Provita Eurotech Ltd
Category: animal | Type: OTC ANIMAL DRUG LABEL
Date: 20230814

ACTIVE INGREDIENTS: FORMIC ACID 608 g/1 L

Provita Hoofsure Endurance Express

VETERINARY INDICATIONS

Management Information

Hoofsure Endurance Express is a scientifically proven proprietary blend of organic acids, essential oils and wetting agents specifically designed and formulated to both clean and care for hooves. It does not contain copper, formaldehyde or antibiotics. Hoofsure Endurance Express is intended for use as part of a hoof maintenance program in conjunction with your veterinarian. Hoof health is dependent on good nutrition, hygiene, management and herd health care. Footbathing is a control measure and not a treatment. To optimize hoof health, a treat and control protocol is recommended. Lame cows should be identified, footbathed regularly and treated with an appropriate product such as Provita Konquest gel and Provita Combat spray.

INACTIVE INGREDIENT

Ingredients

Organic Acids (Acetic and Formic), Water, Ethanol, Alkoxylated Cetyl Alcohol, Laureth-4, Tea-tree Oil, E124, E133.

STORAGE AND HANDLING

Disposal

Hoofsure Endurance Express is not subject to bioaccumulation. After use, spent footbath can be disposed of by landfill or flushing to a slurry lagoon in accordance with local regulations. Not for human use.

Precautions

Danger: Flammable liquid and vapour. Harmful if swallowed. Causes severe skin burns and eye damage. Keep away from heat/ sparks/open flames/hot surfaces — No smoking. Do not breathe dust / fume / gas / mist / vapours / spray. Wear protective gloves/ protective clothing/eye protection/face protection. IF SWALLOWED: Rinse mouth. Do NOT induce vomiting. IF ON SKIN (or hair): Remove/Take off immediately all contaminated clothing. Rinse skin with water/ shower. IF INHALED: Remove victim to fresh air and keep at rest in a position comfortable for breathing. IF IN EYES: Rinse cautiously with water for several minutes. Remove contact lenses, if present and easy to do, continue rinsing. If symptoms persist, immediately call a POISON CENTER or doctor/physician. In case of fire: Use water, carbon dioxide (CO2), foam, dry powder for extinction. Store in a well-ventilated place. Keep cool. Keep out of reach of children. For animal use only. Do not use in galvanised footbaths.

Directions for Use

Dairy Cattle

For footbath use: For optimum results footbath at every milking, every day. Mix Hoofsure Endurance Express 1:100 (equivalent to a 1% solution - e.g. half gallon of Hoofsure Endurance Express with 50 gal clean water in a 50 gal footbath). When required, a 2% or above dilution rate may be used. Place footbath in return alley, not in parlor. Wash dirt and manure off feet prior to walking through the footbath. Ideally, use a pre-wash bath.

Number of cow passes before filling fresh footbath (approximate):
Footbath Capacity | Number of Cow Passes [Ensure footbath solution is at 5" depth or above at all times. Check depth of solution every 200 cows and top up, as necessary, using a top up solution (mix ½ gallon of Hoofsure Endurance Express with 5 gallons of water and add to the footbath. Use of heavily soiled footbaths can become a source of infection or re-infection.]
25 gals | Up to 250
50 gals | Up to 500
100 gals | Up to 1000

For topical application: After inspection or trimming, administer a 25% solution of Hoofsure Endurance Express (i.e. 4 oz Provita Hoofsure Endurance Express mixed with 20 oz of clean water). Using a sprayer, apply to the hoof once per day for up to 3 weeks.

Beef cattle

For footbath use: Footbath every 4-6 weeks. Mix Hoofsure Endurance Express 5:100 (equivalent to a 5% solution - e.g. 5 gallons of Hoofsure Endurance Express with 100 gal clean water in a 100 gal footbath). Wash dirt and manure off feet prior to walking through the footbath. A 100 gal footbath can have 1000 cow passes before needing filled fresh.

Ensure footbath solution is at 5" depth or above at all times. Check depth of solution every 200 cows and top up, as necessary, using a top up solution (mix ½ gallon of Hoofsure Endurance Express with 5 gallons of water and add to the footbath. Use of heavily soiled footbaths can become a source of infection or re-infection.

For topical application: After inspection or trimming, administer a 25% solution of Hoofsure Endurance Express (i.e. 4 oz Provita Hoofsure Endurance Express mixed with 20 oz of clean water). Using a sprayer, apply to the hoof.

Sheep

For footbath use: Footbath every 2-4 weeks. Mix Hoofsure Endurance Express 1:100 (equivalent to a 1% solution - e.g. half gallon of Hoofsure Endurance Express with 50 gal clean water in a 50 gal footbath). When required, a 2% dilution rate may be used. Walk sheep through footbath 3 times or allow sheep to stand in the solution for a short period. A 50 gal footbath can have up to 1000 sheep passes before needing filled fresh.

Number of sheep passes before filling fresh footbath (approximate):
Footbath Capacity | Number of Sheep Passes [Ensure footbath Express solution is at 3" depth or above at all times. Check depth of solution every 100 sheep and top up, as necessary, using a top up solution (mix ½ gallon of Hoofsure Endurance Express with 5 gallons of water and add to the footbath).]
25gal | Up to 500
50 gal | Up to 1000

For topical application: After inspection or trimming, administer a 25% solution of Hoofsure Endurance Express (i.e. 4 oz Provita Hoofsure Endurance Express mixed with 20 oz of clean water). Using sprayer, apply to the hoof.

PRINCIPAL DISPLAY PANEL - 4.75 Litre Drum Label

Provita
Animal Health Naturally

Hoofsure
Endurance
EXPRESS
A footbath solution for healthy hooves
and to aid in the control of footrot

NEW
IMPROVED
FORMULA
33% FASTER ACTING

FOR UP TO
2000
SHEEP,
1250
COWS